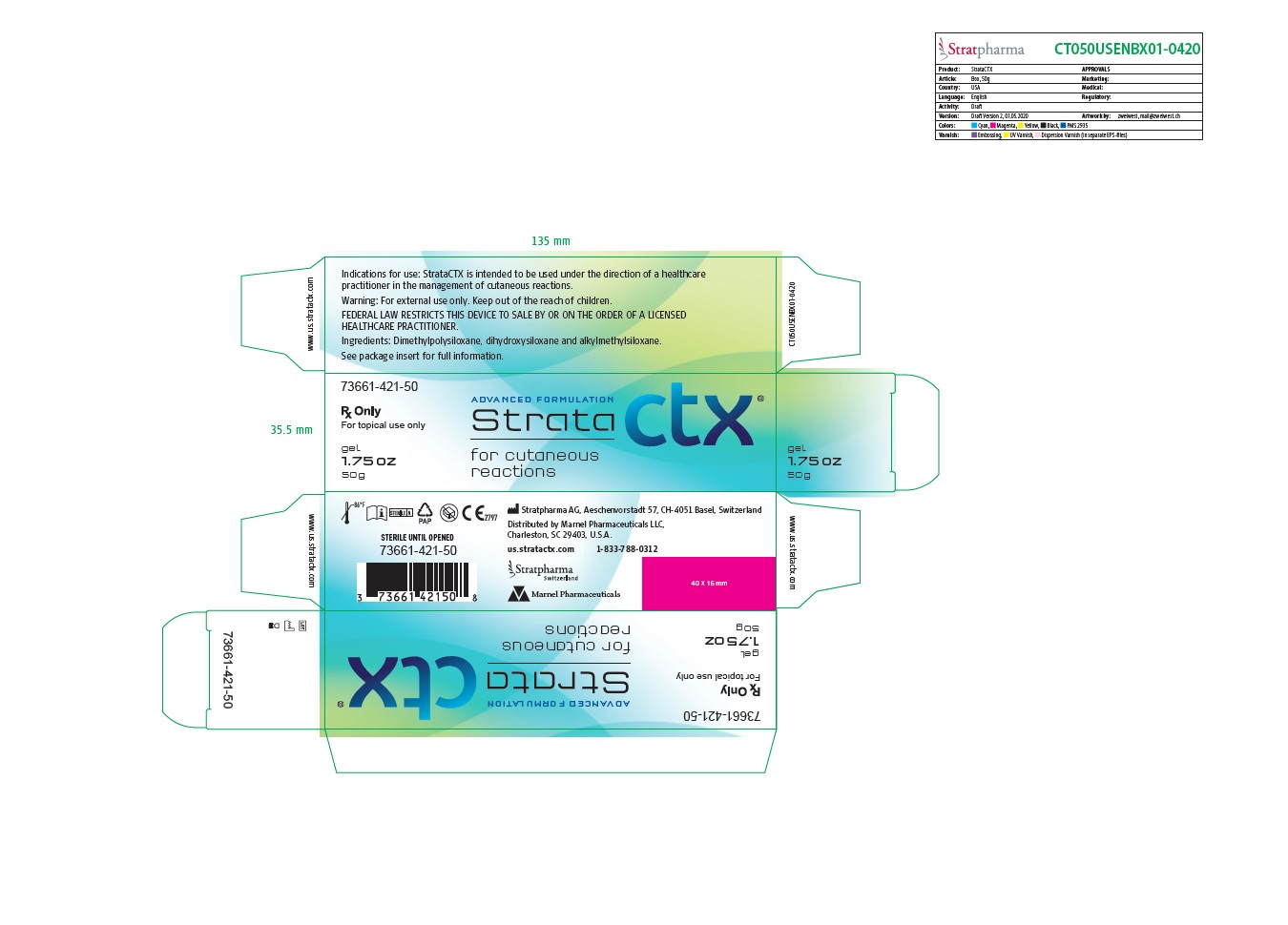 DRUG LABEL: StrataCTX
NDC: 73661-421
Manufacturer: Marnel Pharmaceuticals, Inc.
Category: other | Type: MEDICAL DEVICE
Date: 20200605
INACTIVE INGREDIENTS: DIMETHICONE; DIMETHICONOL (2000 CST); DIDECYLDIMONIUM CHLORIDE

StrataCTX

WARNINGS AND PRECAUTIONS

Rx Only

For topical use only

Federal Law restricts this device to sale by or on order of a licensed healthcare practitioner.

[EN] Description

StrataCTX is an occlusive, non-resorbable, self-drying and transparent gel.

When used as directed StrataCTX dries to form a protective layer that is gas permeable and waterproof which hydrates and protects compromised skin areas and superficial wounds from chemical and microbial invation.

StrataCTX helps to promote a moist healing environment.

This moist wound healing environment promotes faster re-epithelialization* and reduces the skin's acute inflammatory response.

StrataCTX is suitable for large surface areas and contoured skin like head, face, hand and foot as well as joints and hairy areas without the need for shaving.

INDICATIONS AND USAGE

Indication for use

StrataCTX is intended to be used under the direction of healthcare practitioners in the management of cutaneous reactions.

StrataCTX is indicated for use on all types of wounds, toxic and compromised skin including:

- Cutaneous reactions
- Pruritic, itchy skin
- Xerotic, dry skin
- Desquamation
- Fissures of skin and nail folds
- Blisters
- Medical Adhesive-Related Skin Injuries (MARSI)
- Erythema
- Infusion reactions
- Rashes, including: Maculopapular rash, hand-foot syndrome, GVHD, acneiform reaction, peri- and appendageal (hair follicles, sweat glands)

StrataCTX is indicated for the relief of dry, itching, flaking, peeling and irritated skin, as well as the symptomatic relief of pain, redness and heat sensation.

StrataCTX may be directly applied to dry skin, open wounds and compromised or desquamating skin surfaces, including cutaneous rashes.

StrataCTX gel is bacteriostatic and inert.

It contains no alcohols, parabens or fragrances.

StrataCTX can be used with or without a secondary protective dressing.

StrataCTX is suitable for children and people with sensitive skin.

StrataCTX is intented for single patient use.

INDICATIONS AND USAGE

Directions for use

On the first use of 1.75 oz (50g) tubes remove the cap, then the protective seal and close with the cap after use.

Ensure that the affected superficial area is clean and dry.

Apply a very thin layer of StrataCTX directly to the affected area and allow the gel to dry.

When applied correctly to exposed areas, StrataCTX should be dry in 5-6 minutes.

If it takes longer to dry you have probably applied too much.

Gently remove the excess with a clean tissue or gauze and allow the drying process to continue.

Once dry, StrataCTX may be covered by sunscreen, cosmetics and clothing.

StrataCTX should be applied at least twice daily to affected areas, as needed or as advised by your physician.

For best results StrataCTX should be maintained in continuous contact with the skin (24 hours a day/7 days a week).

How much StrataCTX do I need?

StrataCTX gel is an advanced formulation that requires substantially less product per application than typical creams or gels.

StrataCTX 1.75 oz (50g) is enough to treat an area of 6x12 inch (15x30 cm) twice per day for 30 days.

Warning:

- For external use only.
- StrataCTX should not be placed in contact with the eyes.
- StrataCTX should not be applied over topical medications unless advised by your physician.
- StrataCTX may stain clothing if not completely dry. If staining occurs, dry cleaning should be able to remove it without damaging the fabric.
- For correct storage please reclose the tube tightly with the cap.
- If irritation occurs, discontinue use and consult your physician.
- Keep out of the reach of children.
- Do not use after the expiration (EXP) date printed on the tube. The expiration (EXP) date does not change once the tube has been opened.
- Do not use if the tube is damaged.

Contraindications:

Do not administer to patients with known hypersensitivity to the ingredients of this product.

STERILE UNTIL OPENED

Ingredients: Dimethylpolysiloxane, dihydroxysiloxane and alkylmethylsiloxane.

How supplied:

StrataCTX 1.75 oz (50g) tube

Product identification code:

73661-421-50